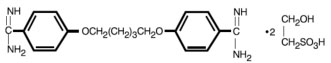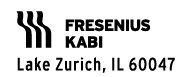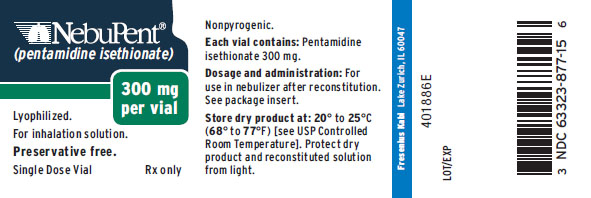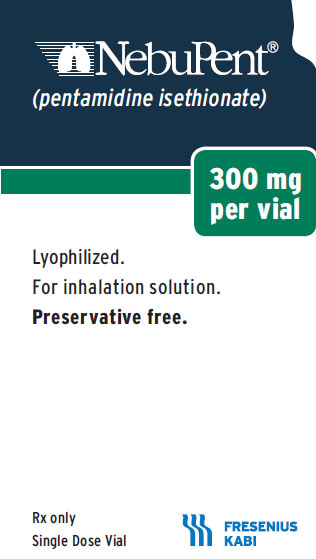 DRUG LABEL: NebuPent
NDC: 63323-877 | Form: INHALANT
Manufacturer: Fresenius Kabi USA, LLC
Category: prescription | Type: HUMAN PRESCRIPTION DRUG LABEL
Date: 20241015

ACTIVE INGREDIENTS: PENTAMIDINE ISETHIONATE 300 mg/6 mL

NebuPent

For Oral Inhalation Only

DESCRIPTION:

NebuPent (pentamidine isethionate), an antifungal agent, is a nonpyrogenic lyophilized product. After reconstitution with Sterile Water for Injection, USP, NebuPent is administered by inhalation via the Respirgard® II nebulizer [Marquest, Englewood, CO] (see DOSAGE AND ADMINISTRATION).

Pentamidine isethionate, 4,4’-[1,5-pentane-diylbis(oxy)]bis-benzenecarboximidamid, is a white crystalline powder soluble in water and glycerin and insoluble in ether, acetone, and chloroform.

C19H24N4O2•2C2H6O4S 592.68

Each vial contains 300 mg pentamidine isethionate.

CLINICAL PHARMACOLOGY:

Microbiology

Mechanism of Action

Studies suggest that the pentamidine isethionate interferes with microbial nuclear metabolism by inhibition of DNA, RNA, phospholipid and protein synthesis. However, the mode of action is not fully understood.

Activity in vitro and in vivo

Pentamidine isethionate, an aromatic diamidine, is known to have activity against Pneumocystis jiroveci.

Pharmacokinetics

In 5 AIDS patients with suspected Pneumocystis jiroveci pneumonia (PJP), the mean concentrations of pentamidine determined 18 to 24 hours after inhalation therapy were 23.2 ng/mL (range 5.1 to 43.0 ng/mL) in bronchoalveolar lavage fluid and 705 ng/mL (range 140 to 1336 ng/mL) in sediment after administration of a 300 mg single dose via the Respirgard® II nebulizer. In 3 AIDS patients with suspected PJP, the mean concentrations of pentamidine determined 18 to 24 hours after a 4 mg/kg intravenous dose were 2.6 ng/mL (range 1.5 to 4.0 ng/mL) in bronchoalveolar lavage fluid and 9.3 ng/mL (range 6.9 to 12.8 ng/mL) in sediment. In the patients who received aerosolized pentamidine, the peak plasma levels of pentamidine were at or below the lower limit of detection of the assay (2.3 ng/mL).

Following a single 2-hour intravenous infusion of 4 mg/kg of pentamidine isethionate to 6 AIDS patients, the mean plasma Cmax, T 1/2 and clearance were 612 ± 371 ng/mL, 6.4 ± 1.3 hr and 248 ± 91 L/hr respectively. In another study of aerosolized pentamidine in 13 AIDS patients with acute PJP who received 4 mg/kg/day administered via the Ultra Vent® jet nebulizer, peak plasma levels of pentamidine averaged 18.8 ± 11.9 ng/mL after the first dose. During the next 14 days of repeated dosing, the highest observed Cmax averaged 20.5 ± 21.2 ng/mL. In a third study, following daily administration of 600 mg of inhaled pentamidine isethionate with the Respirgard® II nebulizer for 21 days in 11 patients with acute PJP, mean plasma levels measured shortly after the 21st dose averaged 11.8 ± 10.0 ng/mL. Plasma concentrations after aerosol administration are substantially lower than those observed after a comparable intravenous dose. The extent of pentamidine accumulation and distribution following chronic inhalation therapy are not known.

In rats, intravenous administration of a 5 mg/kg dose resulted in concentrations of pentamidine in the liver and kidney that were 87.5 and 62.3-fold higher, respectively, than levels in those organs following 5 mg/kg administered as an aerosol.

No pharmacokinetic data are available following aerosol administration of pentamidine in humans with impaired hepatic or renal function.

INDICATIONS AND USAGE:

NebuPent is indicated for the prevention of Pneumocystis jiroveci pneumonia (PJP) in high-risk, HIV-infected patients defined by one or both of the following criteria:

i. a history of one or more episodes of PJP

ii. a peripheral CD4+ (T4 helper/inducer) lymphocyte count less than or equal to 200/mm^3.

These indications are based on the results of an 18-month randomized, dose-response trial in high risk HIV-infected patients and on existing epidemiological data from natural history studies.

The patient population of the controlled trial consisted of 408 patients, 237 of whom had a history of one or more episodes of PJP. The remaining patients without a history of PJP included 55 patients with Kaposi’s sarcoma and 116 patients with other AIDS diagnoses, ARC or asymptomatic HIV infection. Patients were randomly assigned to receive NebuPent via the Respirgard® II nebulizer at one of the following three doses: 30 mg every two weeks (n=135), 150 mg every two weeks (n=134) or 300 mg every four weeks (n=139). The results of the trial demonstrated a significant protective effect (p<0.01) against PJP with the 300 mg every four week dosage regimen compared to the 30 mg every two week dosage regimen. The 300 mg dose regimen reduced the risk of developing PJP by 50 to 70% compared to the 30 mg regimen. A total of 293 patients (72% of all patients) also received zidovudine at sometime during the trial. The analysis of the data demonstrated the efficacy of the 300 mg dose even after adjusting for the effect of zidovudine.

The results of the trial further demonstrate that the dose and frequency of dosing are important to the efficacy of NebuPent prophylaxis in that multiple analyses consistently demonstrated a trend toward greater efficacy with 300 mg every four weeks as compared to 150 mg every two weeks.

No dose-response was observed for reduction in overall mortality; however, mortality from PJP was low in all three dosage groups.

CONTRAINDICATIONS:

NebuPent is contraindicated in patients with a history of an anaphylactic reaction to inhaled or parenteral pentamidine isethionate.

WARNINGS:

The potential for development of acute PJP still exists in patients receiving NebuPent prophylaxis. Therefore, any patient with symptoms suggestive of the presence of a pulmonary infection, including but not limited to dyspnea, fever or cough, should receive a thorough medical evaluation and appropriate diagnostic tests for possible acute PJP as well as for other opportunistic and nonopportunistic pathogens. The use of NebuPent may alter the clinical and radiographic features of PJP and could result in an atypical presentation, including but not limited to mild disease or focal infection.

Prior to initiating NebuPent prophylaxis, symptomatic patients should be evaluated appropriately to exclude the presence of PJP. The recommended dose of NebuPent for the prevention of PJP is insufficient to treat acute PJP.

PRECAUTIONS:

IMPORTANT: DO NOT MIX THE NEBUPENT SOLUTION WITH ANY OTHER DRUGS. DO NOT USE THE RESPIRGARD® II NEBULIZER TO ADMINISTER A BRONCHODILATOR. (See DOSAGE AND ADMINISTRATION).

Pulmonary

Inhalation of NebuPent may induce bronchospasm or cough. This has been noted particularly in some patients who have a history of smoking or asthma. In clinical trials, cough and bronchospasm were the most frequently reported adverse experiences associated with NebuPent administration (38% and 15%, respectively of patients receiving the 300 mg dose); however less than 1% of the doses were interrupted or terminated due to these effects. For the majority of patients, cough and bronchospasm were controlled by administration of an aerosolized bronchodilator (only 1% of patients withdrew from the study due to treatment-associated cough or bronchospasm). In patients who experience bronchospasm or cough, administration of an inhaled bronchodilator prior to giving each NebuPent dose may minimize recurrence of the symptoms.

General

The extent and consequence of pentamidine accumulation following chronic inhalation therapy are not known. As a result, patients receiving NebuPent should be closely monitored for the development of serious adverse reactions that have occurred in patients receiving parenteral pentamidine, including hypotension, hypoglycemia, hyperglycemia, hypocalcemia, anemia, thrombocytopenia, leukopenia, hepatic or renal dysfunction, ventricular tachycardia, pancreatitis, Stevens-Johnson syndrome, hyperkalemia and abnormal ST segment of ECG.

Extrapulmonary infection with P. jiroveci has been reported infrequently. Most, but not all, of the cases have been reported in patients who have a history of PJP. The presence of extrapulmonary pneumocystosis should be considered when evaluating patients with unexplained signs and symptoms.

Cases of acute pancreatitis have been reported in patients receiving aerosolized pentamidine. NebuPent should be discontinued if signs or symptoms of acute pancreatitis develop.

Drug Interactions

While specific studies on drug interactions with NebuPent have not been conducted, the majority of patients in clinical trials received concomitant medications, including zidovudine, with no reported interactions. Because the nephrotoxic effects may be additive, the concomitant or sequential use of NebuPent and other nephrotoxic drugs such as aminoglycosides, amphotericin B, cisplatin, foscarnet, or vancomycin should be closely monitored and avoided, if possible.

Carcinogenesis, Mutagenesis and Impairment of Fertility

Literature reports indicate that pentamidine was not mutagenic in the Ames bacterial (S. typhimurium) test and did not induce an increase in chromosomal aberrations in Chinese Hamster Ovary (CHO) cell or in human lymphocytes in vitro.

No studies have been conducted to determine effects of pentamidine isethionate on carcinogenicity or fertility.

Pregnancy-Pregnancy Category C

There are no adequate and well controlled studies of NebuPent in pregnant women. A literature report indicated that intravenously administered pentamidine in pregnant rats at 4 mg/kg/day was embryolethal; teratogenicity was not observed in this study. It is unknown whether pentamidine administered via the aerosolized route crosses the placenta at clinically significant concentrations. It is not known whether NebuPent can cause fetal harm when administered to a pregnant woman. NebuPent should be given to a pregnant woman only if clearly needed.

Nursing Mothers

It is not known whether NebuPent is excreted in human milk. Because of the potential for serious adverse reactions in nursing infants from NebuPent, a decision should be made whether to discontinue nursing or to discontinue the drug, taking into account the importance of the drug to the mother. Because many drugs are excreted in human milk, NebuPent should not be given to a nursing mother unless the potential benefits are judged to outweigh the unknown risks.

Pediatric Use

The safety and effectiveness of NebuPent in pediatric patients (birth to 16 years of age) have not been established.

ADVERSE REACTIONS:

The most frequently reported unsolicited adverse events (1 to 5%) in clinical trials, regardless of their relation to NebuPent therapy were as follows (n=931):

Body as a Whole: Night sweats.

Gastrointestinal: Diarrhea and nausea.

Hematologic: Anemia.

Infection: Bronchitis, non-specific herpes, herpes zoster, non-specific influenza, oral Candida, pharyngitis, sinusitis, and upper respiratory tract.

Nervous System: Headache.

Respiratory System: Chest pain, cough, and wheezing.

Special Senses: Bad taste.

Adverse events of less than 1% incidence were as follows (No causal relationship to treatment has been established for these adverse events):

Body as a Whole: Allergic reaction, non-specific allergy, body odor, facial edema, fever, leg edema, lethargy, low body temperature, and temperature abnormality.

Cardiovascular: Cerebrovascular accident, hypotension, hypertension, palpitations, poor circulation, syncope, tachycardia, vasodilatation and vasculitis.

Gastrointestinal: Abdominal cramps, abdominal pain, constipation, dry mouth, dyspepsia, gastritis, gastric ulcer, gingivitis, hiatal hernia, hypersalivation, oral ulcer/abscess, splenomegaly, and vomiting.

Hematological: Eosinophilia, neutropenia, non-specific cytopenia, pancytopenia, and thrombocytopenia.

Hepatic: Hepatitis, hepatomegaly, and hepatic dysfunction.

Infection: Bacterial pneumonia, central venous line related sepsis, cryptococcal meningitis, cytomegalovirus (CMV) colitis, CMV retinitis, esophageal Candida, histoplasmosis, Kaposi’s sarcoma, non-specific mycoplasma, oral herpes, non-specific otitis, non-specific pharyngitis, pharyngeal herpes, non-specific serious infection, tonsillitis, tuberculosis, and viral encephalitis.

Metabolic: Hyperglycemia, hypoglycemia, and hypocalcemia.

Musculoskeletal: Arthralgia, gout, and myalgia.

Neurological: Anxiety, confusion, depression, drowsiness, emotional lability, hallucination, hypesthesia, insomnia, memory loss, neuralgia, neuropathy, non-specific neuropathy, nervousness, paranoia, paresthesia, peripheral neuropathy, seizure, tremors, unsteady gait, and vertigo.

Reproductive: Miscarriage.

Respiratory system: Asthma, bronchitis, bronchospasm, chest congestion, chest tightness, coryza, cyanosis, eosinophilic or interstitial pneumonitis, gagging, hemoptysis, hyperventilation, laryngitis, laryngospasm, non-specific lung disorder, nasal congestion, pleuritis, pneumothorax, rales, rhinitis, shortness of breath, non-specific sputum, and tachypnea.

Skin: Desquamation, dry and breaking hair, dry skin, erythema, non-specific dermatitis, pruritus, rash, and urticaria.

Special senses: Blepharitis, blurred vision, conjunctivitis, contact lens discomfort, eye pain or discomfort, hemianopsia, loss of taste, non-specific odor, and smell.

Urogenital: Flank pain, incontinence, nephritis, renal failure, and renal pain.

In a clinical trial where some adverse events were solicited by investigators, the incidences were as follows:

Cough (62.7%)

Decreased appetite (50.0%)

Dizziness or light-headedness (45.1%)

Fatigue (65.7%)

Fever (51.0%)

Non-specific serious infection (15.2%)

Shortness of breath (48.3%)

Wheezing (32.4%)

From post-marketing clinical experience with NebuPent the following spontaneous adverse events have been reported: anaphylaxis, colitis, diabetes, dyspnea, esophagitis, hematochezia, increased blood urea nitrogen (BUN) and serum creatinine levels, melena, pancreatitis (see WARNINGS), syndrome of inappropriate antidiuretic hormone (SIADH), and torsade de pointes.

OVERDOSAGE:

Overdosage has not been reported with NebuPent. The symptoms and signs of overdosage are not known.

A serious overdosage, to the point of producing systemic drug levels similar to those following parenteral administration, would have the potential of producing similar types of serious systemic toxicity. (See PRECAUTIONS).

Available clinical pharmacology data (see CLINICAL PHARMACOLOGY) suggest that a dose up to 40 times the recommended NebuPent dosage would be required to produce systemic levels similar to a single 4 mg/kg intravenous dose.

DOSAGE AND ADMINISTRATION:

IMPORTANT: NEBUPENT MUST BE DISSOLVED ONLY IN STERILE WATER FOR INJECTION, USP. DO NOT USE SALINE SOLUTION FOR RECONSTITUTION BECAUSE THE DRUG WILL PRECIPITATE. DO NOT MIX THE NEBUPENT SOLUTION WITH ANY OTHER DRUGS. DO NOT USE THE RESPIRGARD® II NEBULIZER TO ADMINISTER A BRONCHODILATOR.

Reconstitution

The contents of one vial (300 mg) must be dissolved in 6 mL Sterile Water for Injection, USP. Place the entire reconstituted contents of the vial into the Respirgard® II nebulizer reservoir for administration.

Dosage

The recommended adult dosage of NebuPent for the prevention of Pneumocystis jiroveci pneumonia is 300 mg once every four weeks administered via the Respirgard® II nebulizer.

The dose should be delivered until the nebulizer chamber is empty (approximately 30 to 45 minutes). The flow rate should be 5 to 7 liters per minute from a 40 to 50 pounds per square inch (PSI) air or oxygen source. Alternatively, a 40 to 50 PSI air compressor can be used with flow limited by setting the flowmeter at 5 to 7 liters per minute or by setting the pressure at 22 to 25 PSI. Low pressure (less than 20 PSI) compressors should not be used.

Stability

Freshly prepared solutions for aerosol use are recommended. After reconstitution with sterile water, the NebuPent solution is stable for 48 hours in the original vial at room temperature if protected from light.

HOW SUPPLIED:

Product No. | NDC No.
87715 | 63323-877-15 | NebuPent® (pentamidine isethionate) 300 mg per vial lyophilized product in single dose vials, individually packaged.

Store dry product at 20° to 25°C (68° to 77°F) [see USP Controlled Room Temperature].

Protect the dry product and the reconstituted solution from light.

www.fresenius-kabi.us

45847E

Revised: October 2016

PACKAGE LABEL

PACKAGE LABEL – PRINCIPAL DISPLAY – NebuPent 300 mg Single Dose Vial Label

NebuPent (pentamidine isethionate)

300 mg per vial

Lyophilized.

For inhalation solution.
Preservative free.

Single Dose Vial

Rx only

PACKAGE LABEL – PRINCIPAL DISPLAY – NebuPent 300 mg Single Dose Vial Carton Panel

NebuPent

(pentamidine isethionate)

300 mg per vial

Lyophilized.

For inhalation solution.
Preservative free.

Rx only
Single Dose Vial